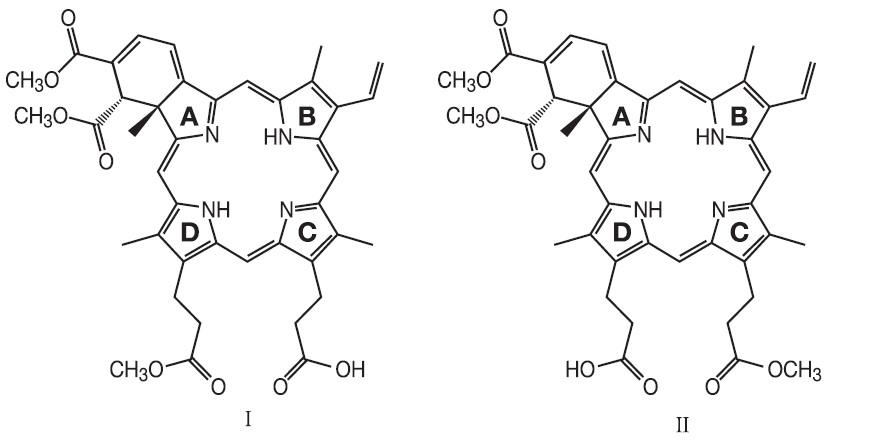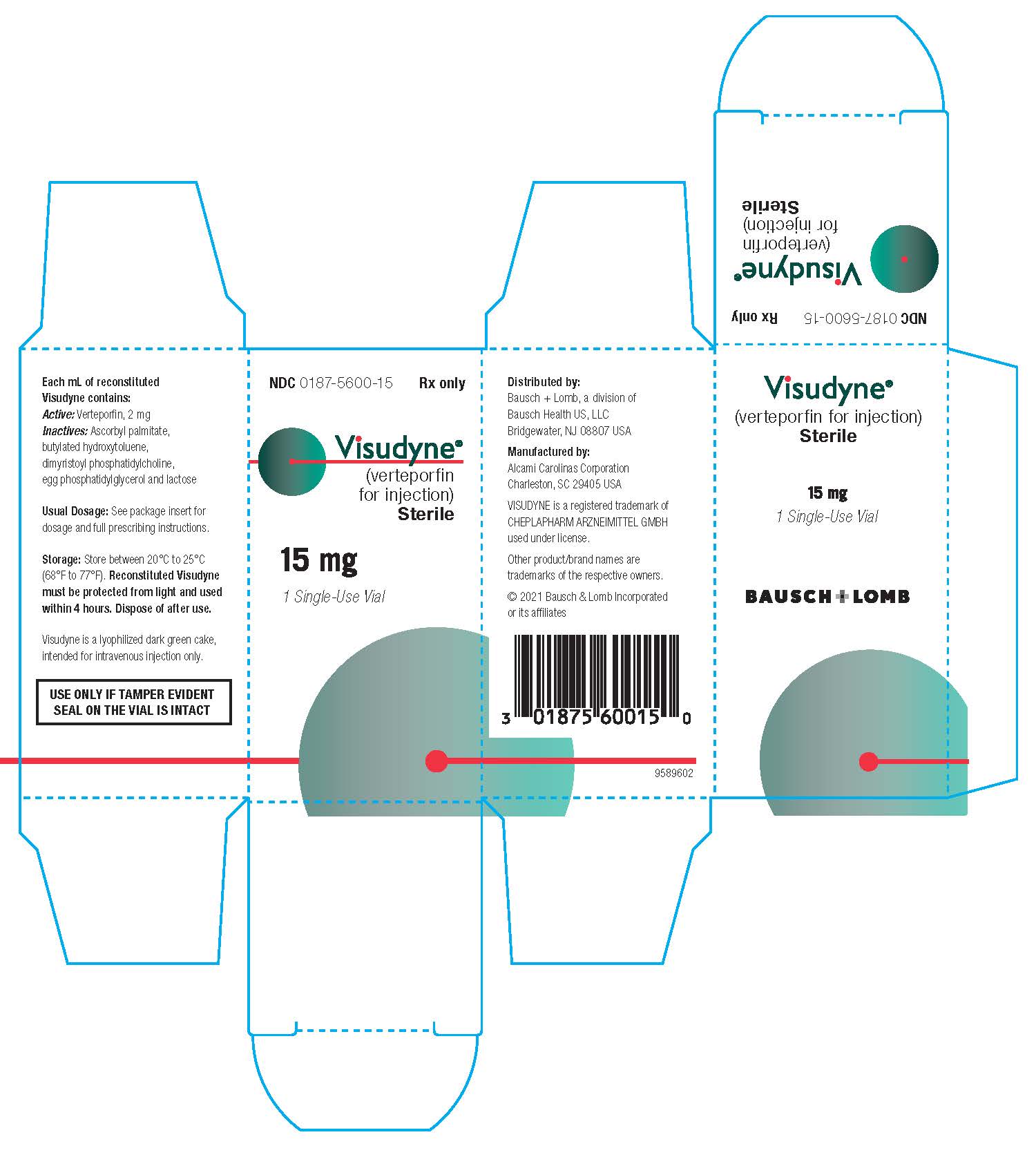 DRUG LABEL: Visudyne
NDC: 0187-5600 | Form: INJECTION, POWDER, LYOPHILIZED, FOR SOLUTION
Manufacturer: Bausch Health US LLC
Category: prescription | Type: HUMAN PRESCRIPTION DRUG LABEL
Date: 20250827

ACTIVE INGREDIENTS: VERTEPORFIN 15 mg/1 1
INACTIVE INGREDIENTS: ASCORBYL PALMITATE; BUTYLATED HYDROXYTOLUENE; LACTOSE, UNSPECIFIED FORM

HIGHLIGHTS OF PRESCRIBING INFORMATION

These highlights do not include all the information needed to use VISUDYNE safely and effectively. See full prescribing information for VISUDYNE.
VISUDYNE®(verteporfin for injection), for intravenous use
Initial U.S. Approval: 2000

RECENT MAJOR CHANGES

Warnings and Precautions (5.1, 5.4) 7/2021

1 INDICATIONS AND USAGE

VISUDYNE (verteporfin for injection) therapy is a photoenhancer indicated for the treatment of patients with predominantly classic subfoveal choroidal neovascularization due to age-related macular degeneration, pathologic myopia or presumed ocular histoplasmosis. (1)

2 DOSAGE AND ADMINISTRATION

- Recommended Dose: 6 mg/m^2body surface area. (2.2)
- Reconstitution: Reconstitute each vial of VISUDYNE with 7 mL of Sterile Water for Injection to provide 7.5 mL containing 2 mg/mL of verteporfin. Reconstituted VISUDYNE must be protected from light and used within 4 hours. (2.3)
- Dilution: Dilute desired dose of reconstituted VISUDYNE with 5% Dextrose for Injection to a total infusion volume of 30 mL. (2.3)
- Infusion: Administer intravenously over 10 minutes at a rate of 3 mL/minute, using an appropriate syringe pump and in-line filter. (2.3)
- Light Administration: The recommended light dose is 50 J/cm^2of neovascular lesion administered at an intensity of 600 mW/cm^2. The wavelength of the laser light should be 689±3 nm. This light dose is administered over 83 seconds, starting 15 minutes after the start of the VISUDYNE infusion. (2.4)

3 DOSAGE FORMS AND STRENGTHS

- For injection: 15 mg of verteporfin as a dark green lyophilized cake in a single-dose vial for reconstitution. (3)
- Each reconstituted vial provides 7.5 mL solution containing 2 mg/mL of verteporfin. (3)

4 CONTRAINDICATIONS

VISUDYNE (verteporfin for injection) is contraindicated for patients with porphyria or a known hypersensitivity to any component of this preparation. (4)

5 WARNINGS AND PRECAUTIONS

- Extravasation: If extravasation occurs, the infusion should be stopped immediately. The extravasation area must be thoroughly protected from direct light until swelling and discoloration have faded in order to prevent the occurrence of local burn. (5.1)
- Exposure to Sun or Direct Light: Following injection with VISUDYNE (verteporfin for injection), care should be taken to avoid exposure of skin or eyes to direct sunlight or bright indoor light for 5 days. (5.2)
- Anaphylactic Reactions: Immediately discontinue administration of VISUDYNE and initiate appropriate therapy if an anaphylactic or other serious allergic reaction occurs during or following infusion. (5.4)

6 ADVERSE REACTIONS

Most common adverse reactions (incidence ˃10%) are injection site reactions and visual disturbances. (6.1)

To report SUSPECTED ADVERSE REACTIONS, contact Bausch & Lomb Incorporated at 1-800-321-4576 or FDA at 1-800-FDA-1088 or www.fda.gov/medwatch.

FULL PRESCRIBING INFORMATION

1 INDICATIONS AND USAGE

VISUDYNE®(verteporfin for injection) therapy is indicated for the treatment of patients with predominantly classic subfoveal choroidal neovascularization (CNV) due to age-related macular degeneration (AMD), pathologic myopia or presumed ocular histoplasmosis.

There is insufficient evidence to indicate VISUDYNE for the treatment of predominantly occult subfoveal CNV.

2 DOSAGE AND ADMINISTRATION

2.1 Important Administration Instructions

A course of VISUDYNE (verteporfin for injection) therapy is a two-step process requiring administration of both drug and light.

- The first step is the administration of VISUDYNE.
- The second step is the activation of VISUDYNE with light from a nonthermal diode laser.

The physician should re-evaluate the patient 3 months after treatment and if choroidal neovascular leakage is detected on fluorescein angiography, therapy may be repeated.

Lesion Size Determination

The greatest linear dimension (GLD) of the lesion should be estimated by fluorescein angiography and color fundus photography. All classic and occult CNV, blood and/or blocked fluorescence, and any serous detachments of the retinal pigment epithelium should be included for this measurement. Fundus cameras with magnification within the range of 2.4-2.6X are recommended. The GLD of the lesion on the fluorescein angiogram must be corrected for the magnification of the fundus camera to obtain the GLD of the lesion on the retina.

Spot Size Determination

The treatment spot size should be 1,000 microns larger than the GLD of the lesion on the retina to allow a 500 micron border, ensuring full coverage of the lesion. The maximum spot size used in the clinical trials was 6,400 microns.

The nasal edge of the treatment spot must be positioned at least 200 microns from the temporal edge of the optic disc, even if this will result in lack of photoactivation of CNV within 200 microns of the optic nerve.

2.2 Recommended Dosage of VISUDYNE

The recommended dose of VISUDYNE is 6 mg/m^2body surface area.

2.3 VISUDYNE Administration

Avoid contact with the eyes and skin during preparation and administration of VISUDYNE. Because of the potential to induce photosensitivity reactions, any exposed person must be protected from bright light [see Warnings and Precautions(5.1) and How Supplied/Storage and Handling(16)] .

Reconstitution

Reconstitute each vial of VISUDYNE with 7 mL of Sterile Water for Injection. Each reconstituted vial provides 7.5 mL solution containing 2 mg/mL of verteporfin. Reconstituted VISUDYNE must be protected from light and used within 4 hours. Parenteral drug products should be inspected visually for particulate matter and discoloration prior to administration, whenever solution and container permit. Reconstituted VISUDYNE is an opaque dark green solution.

Dilution

VISUDYNE may precipitate in saline solutions. Do not use normal saline or other parenteral solutions, except 5% Dextrose for Injection, for dilution of the reconstituted VISUDYNE. Do not mix VISUDYNE in the same solution with other drugs.

The volume of reconstituted VISUDYNE required to achieve the desired dose of 6 mg/m^2body surface area is withdrawn from the vial and diluted with 5% Dextrose for Injection to a total infusion volume of 30 mL. After dilution, protect from light and use within 4 hours.

Intravenous Infusion

The full infusion volume is administered intravenously over 10 minutes at a rate of 3 mL/minute, using an appropriate syringe pump and in-line filter. The clinical studies were conducted using a standard infusion line filter of 1.2 microns.

Precautions should be taken to prevent extravasation at the injection site. If extravasation occurs, protect the site from light [see Warnings and Precautions(5.1)] .

2.4 Light Administration

Initiate 689 nm wavelength laser light delivery to the patient 15 minutes after the start of the 10-minute infusion with VISUDYNE.

Photoactivation of VISUDYNE is controlled by the total light dose delivered. In the treatment of CNV, the recommended light dose is 50 J/cm^2of neovascular lesion administered at an intensity of 600 mW/cm^2. This dose is administered over 83 seconds.

Light dose, light intensity, ophthalmic lens magnification factor and zoom lens setting are important parameters for the appropriate delivery of light to the predetermined treatment spot. Follow the laser system manuals for procedure set up and operations.

The laser system must deliver a stable power output at a wavelength of 689±3 nm. Light is delivered to the retina as a single circular spot via a fiber optic and a slit lamp, using a suitable ophthalmic magnification lens.

The following laser systems have been tested for compatibility with VISUDYNE and are approved for delivery of a stable power output at a wavelength of 689±3 nm:

- Coherent Opal Photoactivator laser console and modified Coherent LaserLink adapter, manufactured by Lumenis, Inc., 2400 Condensa Street, Santa Clara, CA 95051-0901,
- Zeiss VISULAS 690s laser and VISULINK PDT adapter manufactured by Carl Zeiss Meditec Inc., 5160 Hacienda Drive, Dublin, CA 94568,
- Ceralas I laser system and Ceralink Slit Lamp Adapter manufactured by Biolitec Inc., 515 Shaker Road, East Longmeadow, MA 01028,
- Quantel Activis laser console and the ZSL30 ACT, ZSL120 ACT and HSBMBQ ACT slit lamp adapters distributed by Quantel Medical, 601 Haggerty Lane, Bozeman, MT 59715.

2.5 Concurrent Bilateral Treatment

The controlled trials only allowed treatment of one eye per patient. In patients who present with eligible lesions in both eyes, physicians should evaluate the potential benefits and risks of treating both eyes concurrently. If the patient has already received previous VISUDYNE therapy in one eye with an acceptable safety profile, both eyes can be treated concurrently after a single administration of VISUDYNE. The more aggressive lesion should be treated first, at 15 minutes after the start of infusion. Immediately at the end of light application to the first eye, the laser settings should be adjusted to introduce the treatment parameters for the second eye, with the same light dose and intensity as for the first eye, starting no later than 20 minutes from the start of infusion.

In patients who present for the first time with eligible lesions in both eyes without prior VISUDYNE therapy, it is prudent to treat only one eye (the most aggressive lesion) at the first course. One week after the first course, if no significant safety issues are identified, the second eye can be treated using the same treatment regimen after a second VISUDYNE infusion. Approximately 3 months later, both eyes can be evaluated and concurrent treatment following a new VISUDYNE infusion can be started if both lesions still show evidence of leakage.

3 DOSAGE FORMS AND STRENGTHS

For injection: 15 mg of verteporfin as a dark green lyophilized cake in a single-dose vial for reconstitution. VISUDYNE is intended for intravenous injection only. Each reconstituted vial provides 7.5 mL solution containing 2 mg/mL of verteporfin.

4 CONTRAINDICATIONS

VISUDYNE (verteporfin for injection) is contraindicated for patients with porphyria or a known hypersensitivity to any component of this preparation [see Adverse Reactions(6)] .

5 WARNINGS AND PRECAUTIONS

5.1 Local Adverse Reactions - Extravasation

Standard precautions should be taken during infusion of VISUDYNE (verteporfin for injection) to avoid extravasation. Examples of standard precautions include, but are not limited to:

- A free-flowing intravenous (IV) line should be established before starting VISUDYNE infusion and the line should be carefully monitored.
- Due to the possible fragility of vein walls of some elderly patients, it is strongly recommended that the largest arm vein possible, preferably antecubital, be used for injection.
- Small veins in the back of the hand should be avoided.

Extravasation of VISUDYNE, especially if the affected area is exposed to light, can cause severe pain, inflammation, swelling or discoloration at the injection site. Localized (skin) necrosis at the injection site following extravasation has also been reported.

If extravasation does occur, the infusion should be stopped immediately. The extravasation area must be thoroughly protected from direct light until swelling and discoloration have faded in order to prevent the occurrence of local burn, which could be severe. Cold compresses should be applied to the injection site. Oral medications for pain relief may be administered.

5.2 Exposure to Sun or Direct Light

Following injection with VISUDYNE (verteporfin for injection), care should be taken to avoid exposure of skin or eyes to direct sunlight or bright indoor light for 5 days. In the event of extravasation during infusion, the extravasation area must be thoroughly protected from direct light until the swelling and discoloration have faded in order to prevent the occurrence of a local burn which could be severe. If emergency surgery is necessary within 48 hours after treatment, as much of the internal tissue as possible should be protected from intense light.

5.3 Decreased Vision After Treatment

Patients who experience severe decrease of vision of 4 lines or more within 1 week after treatment should not be retreated, at least until their vision completely recovers to pretreatment levels and the potential benefits and risks of subsequent treatment are carefully considered by the treating physician.

5.4 Anaphylactic Reactions

Cases of anaphylactic reactions have been reported in patients receiving VISUDYNE. Medical supervision is recommended during infusion. If an anaphylactic or other serious allergic reaction occurs during or following infusion, administration of VISUDYNE should be discontinued immediately and appropriate therapy should be initiated.

6 ADVERSE REACTIONS

The following serious adverse reactions are described elsewhere in the labeling:

- Local Adverse Reactions – Extravasation [see Warnings and Precautions(5.1)]
- Exposure to Sun or Direct Light [see Warnings and Precautions(5.2)]
- Decreased Vision after Treatment [see Warnings and Precautions(5.3)]
- Porphyria and Hypersensitivity [see Contraindications(4)]

6.1 Clinical Trials Experience

Because clinical trials are conducted under widely varying conditions, adverse reaction rates observed in the clinical trials of a drug cannot be directly compared to rates in the clinical trials of another drug and may not reflect the rates observed in practice.

Severe chest pain, vasovagal and hypersensitivity reactions have been reported. Vasovagal and hypersensitivity reactions on rare occasions can be severe. These reactions may include syncope, sweating, dizziness, rash, dyspnea, flushing and changes in blood pressure and heart rate. General symptoms can include headache, malaise, urticaria, and pruritus.

The most frequently reported adverse reactions to VISUDYNE (verteporfin for injection) are injection site reactions (including pain, edema, inflammation, extravasation, rashes, hemorrhage and discoloration) and visual disturbances (including blurred vision, flashes of light, decreased visual acuity and visual field defects, including scotoma). These events occurred in approximately 10%-30% of patients. The following events, listed by Body System, were reported more frequently with VISUDYNE therapy than with placebo therapy and occurred in 1%-10% of patients:

Ocular Treatment Site: Blepharitis, cataracts, conjunctivitis/conjunctival injection, dry eyes, ocular
itching, severe vision decrease with or without subretinal/retinal or vitreous
hemorrhage

Body as a Whole: Asthenia, fever, flu syndrome, infusion related pain primarily presenting as
back pain, photosensitivity reactions

Cardiovascular: Atrial fibrillation, hypertension, peripheral vascular disorder, varicose veins

Dermatologic: Eczema

Digestive: Constipation, gastrointestinal cancers, nausea

Hemic and Lymphatic: Anemia, white blood cell count decreased, white blood cell count increased

Hepatic: Elevated liver function tests

Metabolic/Nutritional: Albuminuria, creatinine increased

Musculoskeletal: Arthralgia, arthrosis, myasthenia

Nervous System: Hypesthesia, sleep disorder, vertigo

Respiratory: Cough, pharyngitis, pneumonia

Special Senses: Cataracts, decreased hearing, diplopia, lacrimation disorder

Urogenital: Prostatic disorder

Severe vision decrease, equivalent of >4 lines, within 7 days after treatment has been reported in 1%-5% of patients. Partial recovery of vision was observed in some patients. Photosensitivity reactions usually occurred in the form of skin sunburn following exposure to sunlight. The higher incidence of back pain in the VISUDYNE group occurred primarily during infusion.

The following adverse events have occurred either at low incidence (<1%) during clinical trials or have been reported during the use of VISUDYNE in clinical practice where these reactions were reported voluntarily from a population of unknown size and frequency of occurrence cannot be determined precisely. They have been chosen for inclusion based on factors such as seriousness, frequency of reporting, possible causal connection to VISUDYNE, or a combination of these factors:

Ocular Treatment Site: Retinal detachment (nonrhegmatogenous), retinal or choroidal vessel
nonperfusion, retinal pigment epithelial tear.

Non-ocular Events: Chest pain and other musculoskeletal pain during infusion, anaphylactic
reaction during or following infusion, injection site necrosis.

7 DRUG INTERACTIONS

Drug interaction studies in humans have not been conducted with VISUDYNE.

Verteporfin is rapidly eliminated by the liver, mainly as unchanged drug. Metabolism is limited and occurs by liver and plasma esterases. Microsomal cytochrome P450 does not appear to play a role in verteporfin metabolism.

Based on the mechanism of action of verteporfin, many drugs used concomitantly could influence the effect of VISUDYNE therapy. Possible examples include the following:

Calcium channel blockers, polymyxin B or radiation therapy could enhance the rate of VISUDYNE uptake by the vascular endothelium. Other photosensitizing agents (e.g., tetracyclines, sulfonamides, phenothiazines, sulfonylurea hypoglycemic agents, thiazide diuretics and griseofulvin) could increase the potential for skin photosensitivity reactions. Compounds that quench active oxygen species or scavenge radicals, such as dimethyl sulfoxide, β-carotene, ethanol, formate and mannitol, would be expected to decrease VISUDYNE activity. Drugs that decrease clotting, vasoconstriction or platelet aggregation, e.g., thromboxane A2 inhibitors, could also decrease the efficacy of VISUDYNE therapy.

8 USE IN SPECIFIC POPULATIONS

8.1 Pregnancy

Risk Summary

There are no data with the use of VISUDYNE in pregnant women to inform a drug-associated risk. Intravenous administration of verteporfin to pregnant rats during the period of organogenesis produced an increase in the incidence of anophthalmia/microphthalmia and wavy ribs at exposures approximately 40-fold the human exposure at the recommended clinical dose.

Verteporfin did not produce adverse fetal effect in rats or rabbits at exposures 6- to 20-fold the human exposure at the recommended clinical dose.

There are no adequate and well-controlled studies in pregnant women. VISUDYNE should be used during pregnancy only if the benefit justifies the potential risk to the fetus.

In the U.S. general population, the estimated background risk of major birth defects and miscarriage in clinically recognized pregnancies is 2%-4% and 15%-20%, respectively.

Data

Animal Data

Rat fetuses of dams administered verteporfin for injection intravenously during organogenesis exhibited an increase in the incidence of anophthalmia/microphthalmia and wavy ribs at doses ≥10 mg/kg/day (approximately 40-fold the human exposure at the recommended dose of 6 mg/m^2, based on AUC in female rats). No teratogenic effects were observed in rat fetuses at a dose of 2 mg/kg/day (approximately 6-fold the human exposure at the recommended dose of 6 mg/m^2, based on AUC in female rats).

In pregnant rabbits, a decrease in maternal body weight gain and food consumption was observed in animals that received verteporfin for injection intravenously at doses up to 10 mg/kg/day during organogenesis. The no observed adverse effect level (NOAEL) for maternal toxicity was 3 mg/kg/day (approximately 6-fold the recommended human dose of 6 mg/m^2, based on body surface area). No teratogenic effects were observed in rabbit fetuses at doses up to 10 mg/kg/day (approximately 20-fold the recommended human dose of 6 mg/m^2, based on body surface area).

8.2 Lactation

Risk Summary

Verteporfin and its diacid metabolite have been found in human breast milk following an intravenous infusion at the recommended human dose of 6 mg/m^2. Verteporfin was present in breast milk at levels up to 66% of the corresponding plasma levels and declined below the limit of quantification (2 ng/mL) within 24 hours. The diacid metabolite had lower peak concentrations but persisted up to at least 48 hours.

Because of the potential for serious adverse reactions in nursing infants from VISUDYNE, a decision should be made whether to discontinue nursing or postpone treatment, taking into account the importance of the drug to the mother.

8.4 Pediatric Use

Safety and effectiveness in pediatric patients have not been established.

8.5 Geriatric Use

Approximately 90% of the patients treated with VISUDYNE in the clinical efficacy trials were over the age of 65. A reduced treatment effect was seen with increasing age.

10 OVERDOSAGE

Overdose of drug and/or light in the treated eye may result in non-perfusion of normal retinal vessels with the possibility of severe decrease in vision that could be permanent. An overdose of drug will also result in the prolongation of the period during which the patient remains photosensitive to bright light. In such cases, it is recommended to extend the photosensitivity precautions for a time proportional to the overdose.

11 DESCRIPTION

VISUDYNE (verteporfin for injection) is a light activated drug used in photodynamic therapy. The finished drug product is a lyophilized dark green cake. Verteporfin is a 1:1 mixture of two regioisomers (I and II), represented by the following structures:

The chemical names for the verteporfin regioisomers are:

9-methyl (I) and 13-methyl (II) trans-(±)-18-ethenyl-4,4a,-dihydro-3,4-bis(methoxycarbonyl)-4a,8,14,19-tetramethyl-23H, 25H-benzo[b]porphine-9,13-dipropanoate

The molecular formula is C41H42N4O8with a molecular weight of approximately 718.8. Each mL of reconstituted VISUDYNE contains:

1. ACTIVE: verteporfin, 2 mg
2. INACTIVES: ascorbyl palmitate, butylated hydroxytoluene, dimyristoyl phosphatidylcholine, egg phosphatidylglycerol and lactose

12 CLINICAL PHARMACOLOGY

12.1 Mechanism of Action

VISUDYNE (verteporfin for injection) therapy is a two-stage process requiring administration of both verteporfin for injection and nonthermal red light.

Verteporfin is transported in the plasma primarily by lipoproteins. Once verteporfin is activated by light in the presence of oxygen, highly reactive, short-lived singlet oxygen and reactive oxygen radicals are generated. Light activation of verteporfin results in local damage to neovascular endothelium, resulting in vessel occlusion. Damaged endothelium is known to release procoagulant and vasoactive factors through the lipoxygenase (leukotriene) and cyclooxygenase (eicosanoids such as thromboxane) pathways, resulting in platelet aggregation, fibrin clot formation and vasoconstriction. Verteporfin appears to somewhat preferentially accumulate in neovasculature, including choroidal neovasculature. However, animal models indicate that the drug is also present in the retina. Therefore, there may be collateral damage to retinal structures following photoactivation including the retinal pigmented epithelium and outer nuclear layer of the retina. The temporary occlusion of the CNV following VISUDYNE therapy has been confirmed in humans by fluorescein angiography.

12.3 Pharmacokinetics

Following intravenous infusion, verteporfin exhibits a bi-exponential elimination with a terminal elimination half-life of approximately 5-6 hours. The extent of exposure and the maximal plasma concentration are proportional to the dose between 6 and 20 mg/m^2. At the intended dose, pharmacokinetic parameters are not significantly affected by gender.

Verteporfin is metabolized to a small extent to its diacid metabolite by liver and plasma esterases. NADPH-dependent liver enzyme systems (including the cytochrome P450 isozymes) do not appear to play a role in the metabolism of verteporfin. Elimination is by the fecal route, with less than 0.01% of the dose recovered in urine.

In a study of patients with mild hepatic insufficiency (defined as having two abnormal hepatic function tests at enrollment), AUC and Cmaxwere not significantly different from the control group; half-life, however, was significantly increased by approximately 20%.

13 NONCLINICAL TOXICOLOGY

13.1 Carcinogenesis, Mutagenesis, Impairment of Fertility

Carcinogenesis
No studies have been conducted to determine the carcinogenic potential of verteporfin.

Mutagenesis
Photodynamic therapy (PDT) as a class has been reported to result in DNA damage including DNA strand breaks, alkali-labile sites, DNA degradation, and DNA-protein cross-links which may result in chromosomal aberrations, sister chromatid exchanges (SCE), and mutations. In addition, other photodynamic therapeutic agents have been shown to increase the incidence of SCE in Chinese hamster ovary (CHO) cells irradiated with visible light and in Chinese hamster lung fibroblasts irradiated with near UV light, increase mutations and DNA-protein cross-linking in mouse L5178 cells, and increase DNA-strand breaks in malignant human cervical carcinoma cells, but not in normal cells. Verteporfin was not evaluated in these latter systems. It is not known how the potential for DNA damage with PDT agents translates into human risk.

Impairment of Fertility
No effect on male or female fertility has been observed in rats following intravenous administration of verteporfin for injection up to 10 mg/kg/day (approximately 60- and 40-fold human exposure at 6 mg/m^2based on AUC in male and female rats, respectively).

13.2 Animal Toxicology and/or Pharmacology

At a >10-fold higher dose given by bolus injection to sedated or anesthetized pigs, verteporfin caused severe hemodynamic effects, including death, probably as a result of complement activation. These effects were diminished or abolished by pretreatment with antihistamine and they were not seen in conscious nonsedated pigs.

14 CLINICAL STUDIES

14.1 Age-Related Macular Degeneration

Two adequate and well-controlled, double-masked, placebo-controlled, randomized studies were conducted in patients with classic-containing subfoveal CNV secondary to AMD. A total of 609 patients (VISUDYNE 402, placebo 207) were enrolled in these two studies. During these studies, retreatment was allowed every 3 months if fluorescein angiograms showed any recurrence or persistence of leakage. The placebo control (sham treatment) consisted of intravenous administration of Dextrose 5% in Water, followed by light application identical to that used for VISUDYNE therapy.

The difference between treatment groups statistically favored VISUDYNE at the 1-year and 2-year analyses for visual acuity endpoints.

The subgroup of patients with predominately classic CNV lesions was more likely to exhibit a treatment benefit (N=242; VISUDYNE 159, placebo 83).

Predominantly classic CNV lesions were defined as those in which the classic component comprised 50% or more of the area of the entire lesion. For the primary efficacy endpoint (percentage of patients who lost less than 3 lines of visual acuity), these patients showed a difference of approximately 28% between treatment groups at both Months 12 and 24 (67% for VISUDYNE patients compared to 40% for placebo patients, at Month 12; and 59% for VISUDYNE patients compared to 31% for placebo patients, at Month 24). Severe vision loss (≥6 lines of visual acuity from baseline) was experienced by 12% of VISUDYNE-treated patients compared to 34% of placebo-treated patients at Month 12, and by 15% of VISUDYNE-treated patients compared to 36% of placebo-treated patients at Month 24.

Patients with predominantly classic CNV lesions that did not contain occult CNV exhibited the greatest benefit (N=134; VISUDYNE 90, placebo 44). At 1 year, these patients demonstrated a 49% difference between treatment groups when assessed by the <3 lines-lost definition (77% vs. 27%).

Older patients (≥75 years), patients with dark irides, patients with occult lesions or patients with less than 50% classic CNV were less likely to benefit from VISUDYNE therapy.

The safety and efficacy of VISUDYNE beyond 2 years have not been demonstrated.

Based on the Treatment of Age Related Macular Degeneration with Photodynamic Therapy Study (TAP) extension study, the average number of treatments per year was 3.5 in the first year after diagnosis, 2.4 in the second, 1.3 in the third, 0.4 in the fourth and 0.1 in the fifth year.

14.2 Pathologic Myopia

One adequate and well-controlled, double-masked, placebo-controlled, randomized study was conducted in patients with subfoveal CNV secondary to pathologic myopia. A total of 120 patients (VISUDYNE 81, placebo 39) were enrolled in the study. The treatment dosing and retreatments were the same as in the AMD studies. The difference between treatment groups statistically favored VISUDYNE at the 1-year analysis but not at the 2-year analysis for visual acuity endpoints. For the primary efficacy endpoint (percentage of patients who lost less than 3 lines of visual acuity), patients at the 1-year timepoint showed a difference of approximately 19% between treatment groups (86% for VISUDYNE patients compared to 67% for placebo patients). However, by the 2-year timepoint, the effect was no longer statistically significant (79% for VISUDYNE patients compared to 72% for placebo patients).

Based on the Verteporfin in Photodynamic Therapy in Pathologic Myopia (VIP-PM) extension study in pathologic myopia, the average number of treatments per year was 3.5 in the first year after diagnosis, 1.8 in the second, 0.4 in the third, 0.2 in the fourth and 0.1 in the fifth.

14.3 Presumed Ocular Histoplasmosis

One open-label study was conducted in patients with subfoveal CNV secondary to presumed ocular histoplasmosis. A total of 26 patients were treated with VISUDYNE in the study. The treatment dosing and retreatments for VISUDYNE were the same as the AMD studies. VISUDYNE-treated patients compare favorably with historical control data demonstrating a reduction in the number of episodes of severe visual acuity loss (>6 lines of loss).

Based on the VISUDYNE Ocular Histoplasmosis extension study in presumed ocular histoplasmosis, the average number of treatments per year was 2.9 in the first year after diagnosis, 1.2 in the second, 0.2 in the third and 0.1 in the fourth.

16 HOW SUPPLIED/STORAGE AND HANDLING

VISUDYNE (verteporfin for injection) is supplied in a single-dose glass vial with a gray bromobutyl stopper and aluminum flip-off cap. It contains a lyophilized dark green cake with 15 mg verteporfin.

- NDC 0187-5600-15

Store VISUDYNE between 20°C to 25°C (68°F to 77°F).

16.1 Spills and Disposal

Spills of VISUDYNE should be wiped up with a damp cloth. Skin and eye contact should be avoided due to the potential for photosensitivity reactions upon exposure to light. Use of rubber gloves and eye protection is recommended. All materials should be disposed of properly.

16.2 Accidental Exposure

Because of the potential to induce photosensitivity reactions, it is important to avoid contact with the eyes and skin during preparation and administration of VISUDYNE. Any exposed person must be protected from bright light [see Warnings and Precautions(5.1)] .

17 PATIENT COUNSELING INFORMATION

Advise patients who receive VISUDYNE that they will become temporarily photosensitive after the infusion. Patients should be advised to wear a wristband to remind them to avoid direct sunlight for 5 days. During that period, patients should be advised to avoid exposure of unprotected skin, eyes or other body organs to direct sunlight or bright indoor light. Sources of bright light include, but are not limited to, tanning salons, bright halogen lighting and high power lighting used in surgical operating rooms or dental offices. Prolonged exposure to light from light-emitting medical devices such as pulse oximeters should also be avoided for 5 days following VISUDYNE administration.

If treated patients must go outdoors in daylight during the first 5 days after treatment, they should be advised to protect all parts of their skin and their eyes by wearing protective clothing and dark sunglasses. UV sunscreens are not effective in protecting against photosensitivity reactions because photoactivation of the residual drug in the skin can be caused by visible light.

Patients should be advised to not stay in the dark and should be encouraged to expose their skin to ambient indoor light, as it will help inactivate the drug in the skin through a process called photobleaching.

Following VISUDYNE treatment, patients should be advised that they may develop visual disturbances such as abnormal vision, vision decrease, or visual field defects that may interfere with their ability to drive or use machines. Patients should be advised to not drive or use machines as long as these symptoms persist.

Distributed by:
Bausch + Lomb, a division of Bausch Health US, LLC
Bridgewater, NJ 08807 USA
Manufactured by:
Alcami Carolinas Corporation
Charleston, SC 29405 USA
VISUDYNE is a registered trademark of CHEPLAPHARM ARZNEIMITTEL GMBH used under license.
Other product/brand names are trademarks of the respective owners.
© 2021 Bausch & Lomb Incorporated or its affiliates

9589702

PACKAGE/LABEL PRINCIPAL DISPLAY PANEL

NDC0187-5600-15

Rx only

Visudyne®
(verteporfin
for injection)
Sterile
15 mg
1 Single-Use Vial